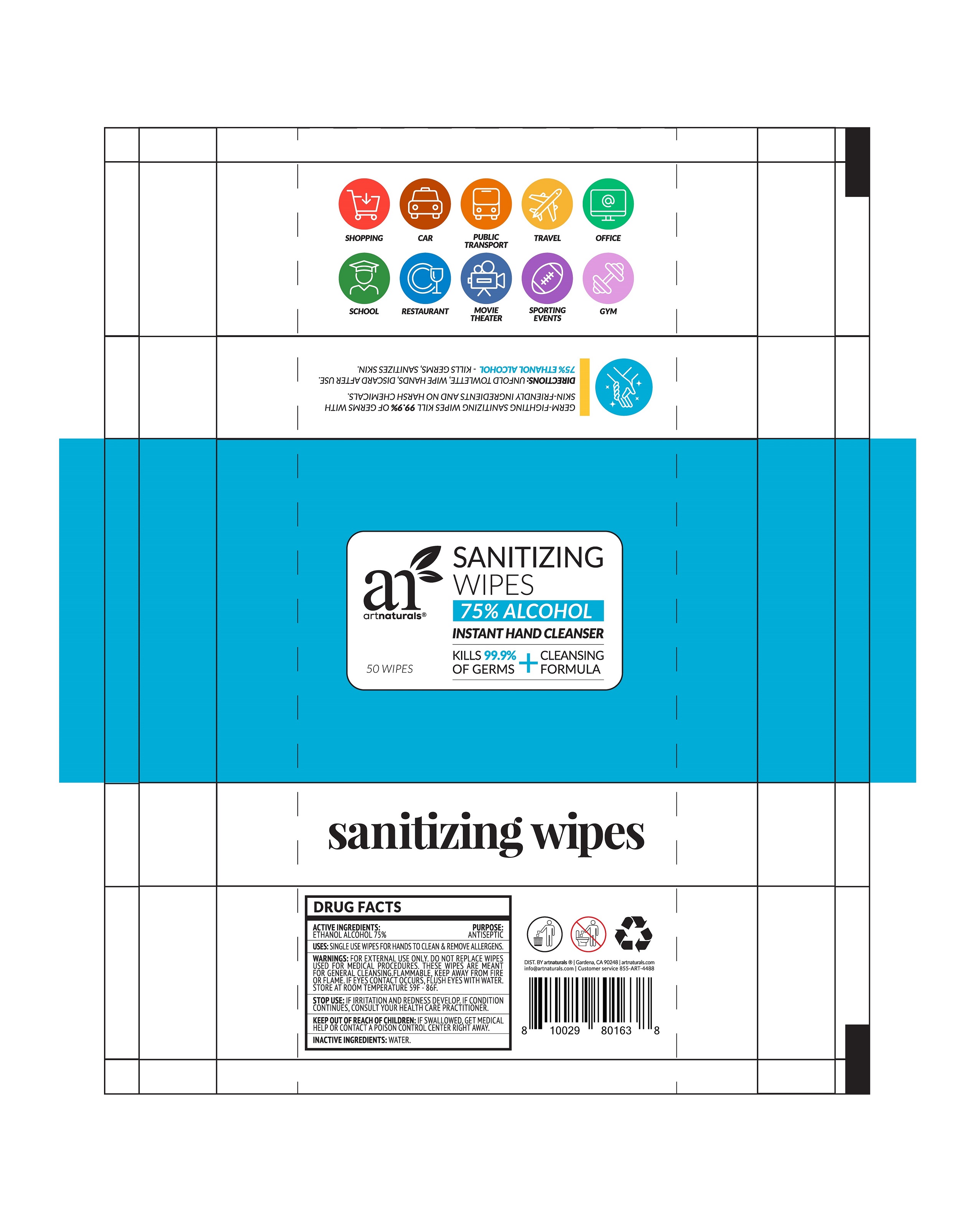 DRUG LABEL: Sanitizing Wipes
NDC: 75163-202 | Form: CLOTH
Manufacturer: Zhuji Jianhe Paper Co., Ltd
Category: otc | Type: HUMAN OTC DRUG LABEL
Date: 20200809

ACTIVE INGREDIENTS: ALCOHOL 26.25 mL/1 1
INACTIVE INGREDIENTS: WATER

JianHe-artnaturals, Sanitizing Wipes, 75% Alcohol, *50 wipes [hide]

Active ingredient

Ethanol Alcohol 75% v/v. Purpose: Antiseptic

Purpose

Antiseptic.

When using

If eyes contact occurs, flush eyes with water.

Do not use

Do not replace wipes used for medical procedures.

Stop use

Stop use if irritation and redness develop. If condition continues, consult your health care practitioner.

Keep out of reach of children

If swallowed, get medical help or contact a Poison Control Center right away.

Indications & usage

Single use wipes for hands to clean & remove allergens.

These wipes are meant for general cleansing.

Directions

Unfold towlette, wipe hands, discard after use.

Warnings

For external use only.

Flammable, keep away from fire or flame.

Other information

Store at room temperature 59℉ - 86℉.

Inactive ingredient

Water.